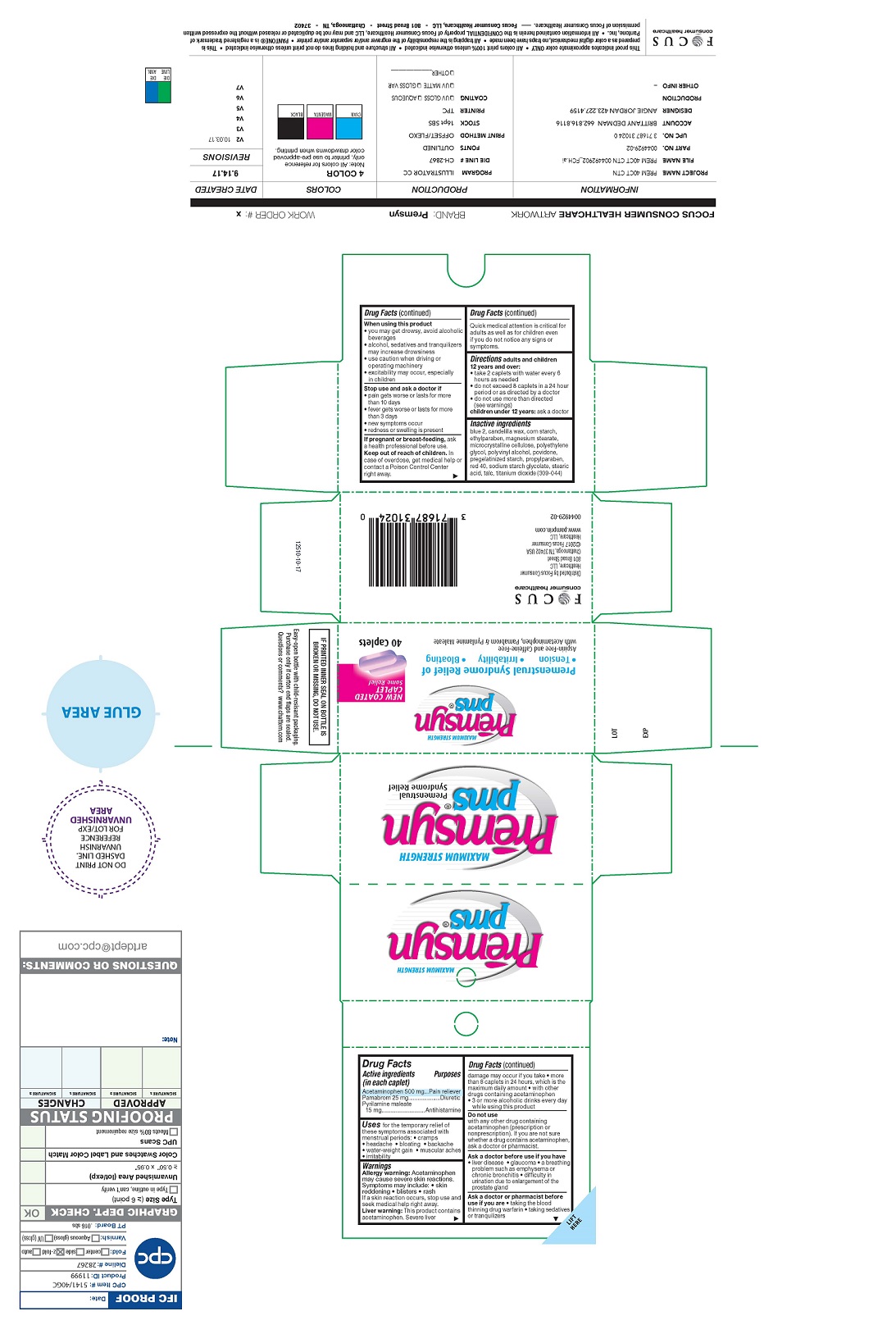 DRUG LABEL: Premsyn pms Premenstrual Pain Relief
NDC: 71687-3102 | Form: TABLET
Manufacturer: Focus Consumer Healthcare, LLC
Category: otc | Type: HUMAN OTC DRUG LABEL
Date: 20250414

ACTIVE INGREDIENTS: ACETAMINOPHEN 500 mg/1 1; PAMABROM 25 mg/1 1; PYRILAMINE MALEATE 15 mg/1 1
INACTIVE INGREDIENTS: CROSPOVIDONE; MAGNESIUM STEARATE; POVIDONE; STEARIC ACID; STARCH, CORN

Premsyn pms Premenstrual Pain Relief

ACTIVE INGREDIENT

(in each caplet)

Acetaminophen 500 mg

Pamabrom 25 mg

Pyrilamine maleate 15 mg

PURPOSE

Pain reliever

Antihistamine

Diuretic

INDICATIONS AND USAGE

For the temporary relief of these symptoms associated with menstrual periods:

- cramps
- headache
- bloating
- backache
- water-weight gain
- muscular aches
- irritability

WARNINGS

Allergy Warning: Acetaminophen may cause severe skin reactions.
Symptoms may include:

- skin reddening
- blisters
- rash

if a skin reaction occurs stop use and seek medical help right away.
Liver warning: This product contains acetaminophen. Severe liver damage may occur if you take
more than 8 caplets in 24 hours, which is the maximum daily amount
with other drugs containing acetaminophen
3 or more alcoholic drinks every day while using this product

Do not use
With any other drug containing acetaminophen (prescription or nonprescription). If you are not sure whether a drug contains acetaminophen, ask a doctor or pharmacist.

Ask a doctor before use if you have:

- liver disease
- glaucoma
- a breathing problem such as emphysema or chronic bronchitis
- difficulty in urination due to enlargment of the prostate gland.

Ask a doctor or pharmacist before use if you are:

- taking the blood thinning drug warfarin
- taking sedatives or tranquilizers
- When using this product,
- you may get drowsy, avoid alcoholic beverages
- alcohol, sedatives and tranquilizers may increase drowsiness
- use caution when driving or operating machinery
- excitability may occur, especially in children

stop use and ask doctor if:

- Pain gets worse or lasts for more than 10 days
- fever gets worse or lasts for more than 3 days
- new symptoms occur
- redness or swelling is present
- If pregnant or breastfeeding, ask a health professional before use.

Do not use

with any other drug containing acetaminophen (prescription or nonprescription). If you are not sure whether a drug contains acetaminophen, ask a doctor or pharmacist.

Ask a doctor before use if

you have

- liver disease
- glaucoma
- a breathing problem such as emphysema or chronic bronchitis
- difficulty in urination due to enlargement of the prostate gland

Ask a doctor or pharmacist before use

if you are

- taking the blood thinning drug warfarin
- taking sedatives or tranquilizers

When using this product

- you may get drowsy, avoid alcoholic beverages
- alcohol, sedatives and tranquilizers may increase drowsiness
- use caution when driving or operating machinery
- excitability may occur, especially in children

Stop use and ask a doctor if

- pain gets worse or lasts for more than 10 days
- fever gets worse or lasts for more than 3 days
- new symptoms occur
- redness or swelling is present

If pregnant or breast-feeding,

ask a health professional before use.

Keep out of reach of children.

In case of overdose, get medical help or contact a Poison Control Center right away. Quick medical attention is critical for adults as well as for children even if you do not notice any signs or symptoms.

Keep out of reach of children. In case of overdose, get medical help or contact a poison control center right away.

Quick medical attention is critical for adults as well as for children even if you do not notice any signs or symptoms.

DOSAGE AND ADMINISTRATION

adults and children 12 years and over:

- take 2 caplets with water every 6 hours as needed
- do not exceed 8 caplets in a 24 hour period or as directed by a doctor
- do not use more than directed (see warnings)

children under 12 years: ask a doctor

INACTIVE INGREDIENT

blue 2, candelilla wax, corn starch, ethylparaben, magnesium stearate, microcrystalline cellulose, polyethylene glycol, polyvinyl alcohol, povidone, pregalatinized starch, propylaparaben, red 40, sodium starch glycolate, stearic acid, talc, titanium dioxide